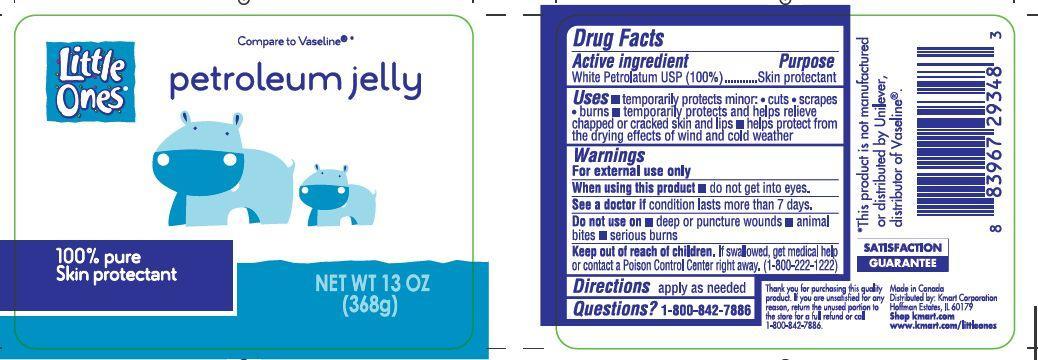 DRUG LABEL: Little Ones Petroleum
NDC: 49738-945 | Form: JELLY
Manufacturer: Kmart Corporation
Category: otc | Type: HUMAN OTC DRUG LABEL
Date: 20121030

ACTIVE INGREDIENTS: Petrolatum 100 g/100 g

Drug Facts

Active Ingredient / Purpose

White Petrolatum USP (100%) ........................... Skin Protectant

Uses

- Temporarily protects minor: cuts, scrapes, burns
- Temporarily protects and helps relieve chapped or cracked skin and lips
- Helps protect from the drying effects of wind and cold weather

Keep out of the reach of children

Use

- Skin protectant.

Warnings

- When using this product do not get into eyes.
- See a doctor if condition lasts more than 7 days.
- Do not use on: deep or puncture wounds, animal bites, serious burns.
- If swallowed, get medical help, or contact a Poison Control Center right away (1-800-222-1222).

Directions

- Apply as needed.

PACKAGE LABEL

mm1